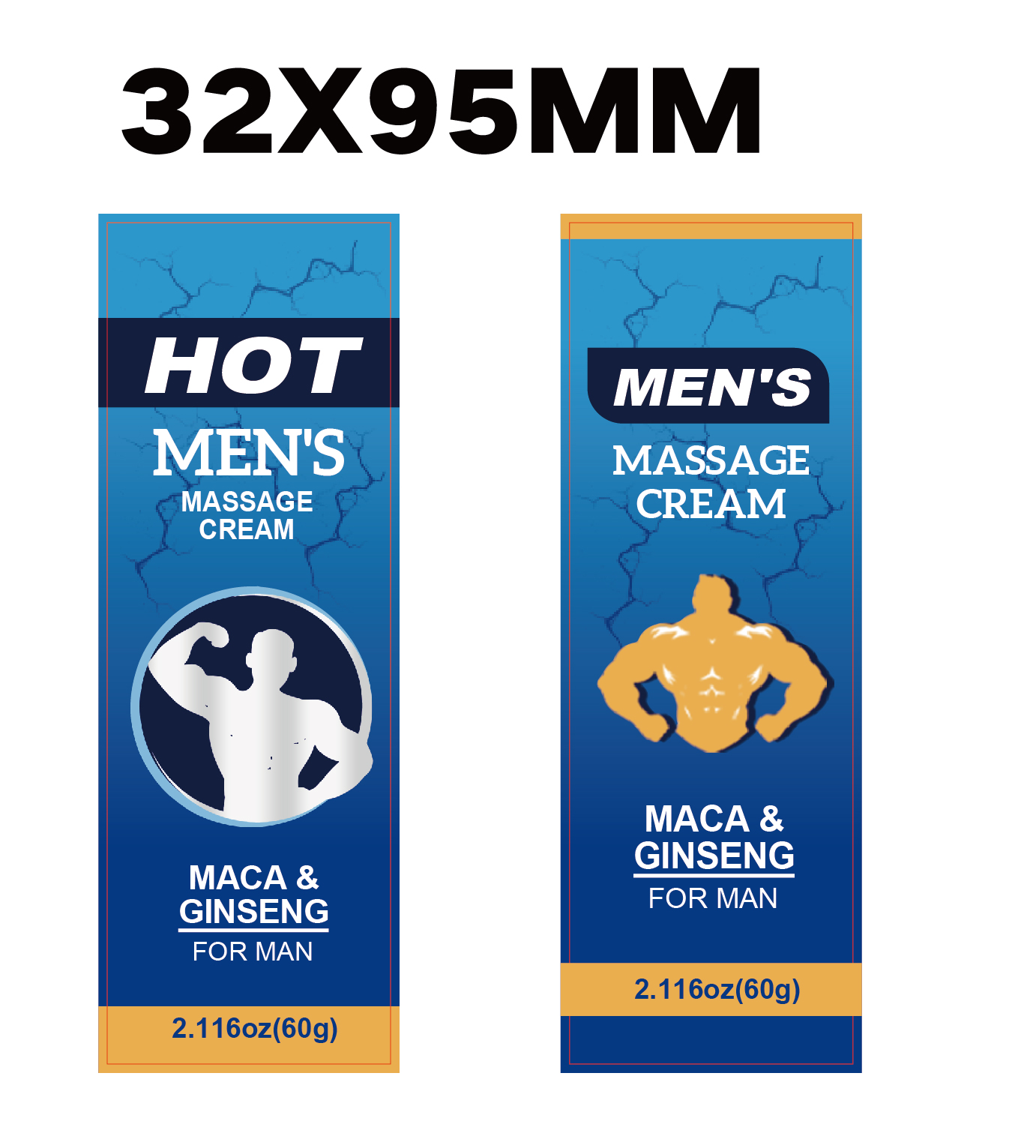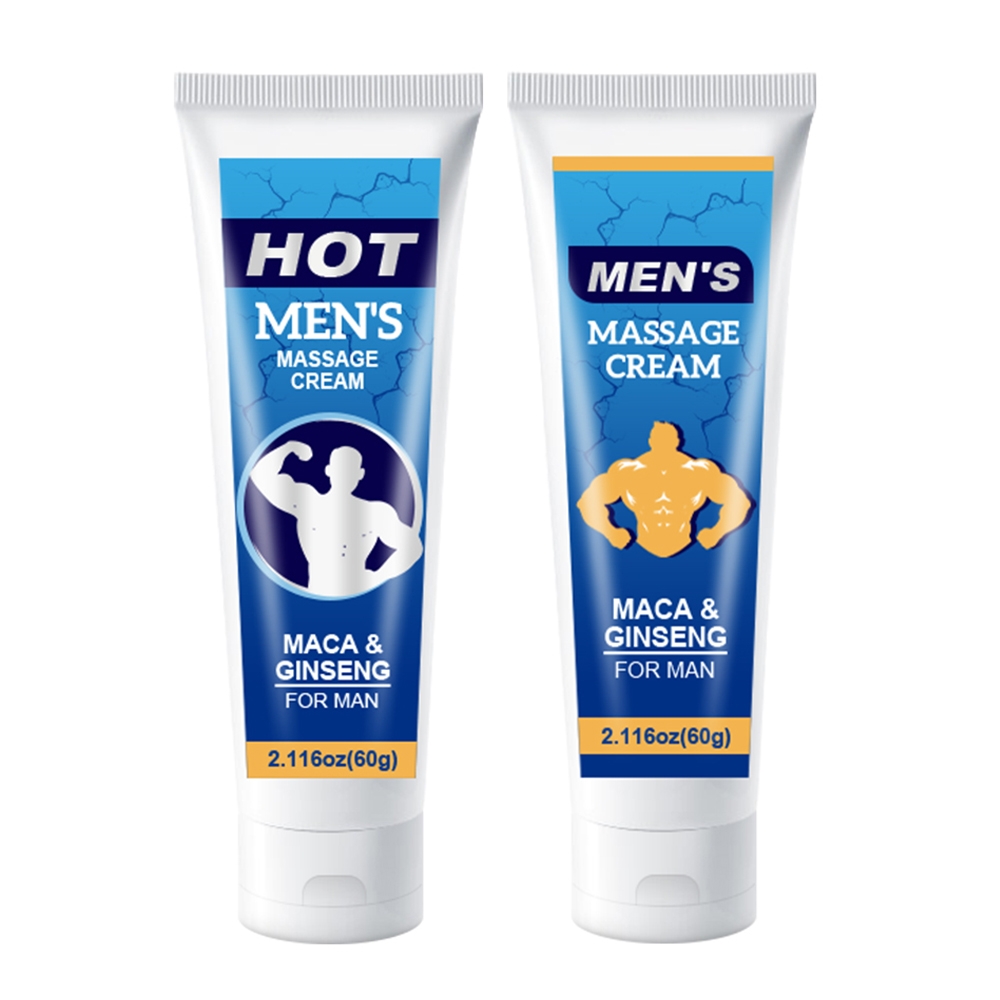 DRUG LABEL: Mens Massage Cream
NDC: 84025-212 | Form: CREAM
Manufacturer: Guangzhou Yanxi Biotechnology Co., Ltd
Category: otc | Type: HUMAN OTC DRUG LABEL
Date: 20241013

ACTIVE INGREDIENTS: PANTHENOL 3 mg/100 mL; GLYCERIN 5 mg/100 mL
INACTIVE INGREDIENTS: WATER

DOSAGE AND ADMINISTRATION

Clean The Private Parts, Squeeze Out The Right Amount Of Cream And Smear The Required Parts.

WARNINGS

keep out of children

INACTIVE INGREDIENT

Aqua

Keep out of children

PURPOSE

The penis erection cream could make the dick thicker, larger, and longer. It can help you to increase feelings of desire and intensify climax.

INDICATIONS AND USAGE

Short duration of sexual function